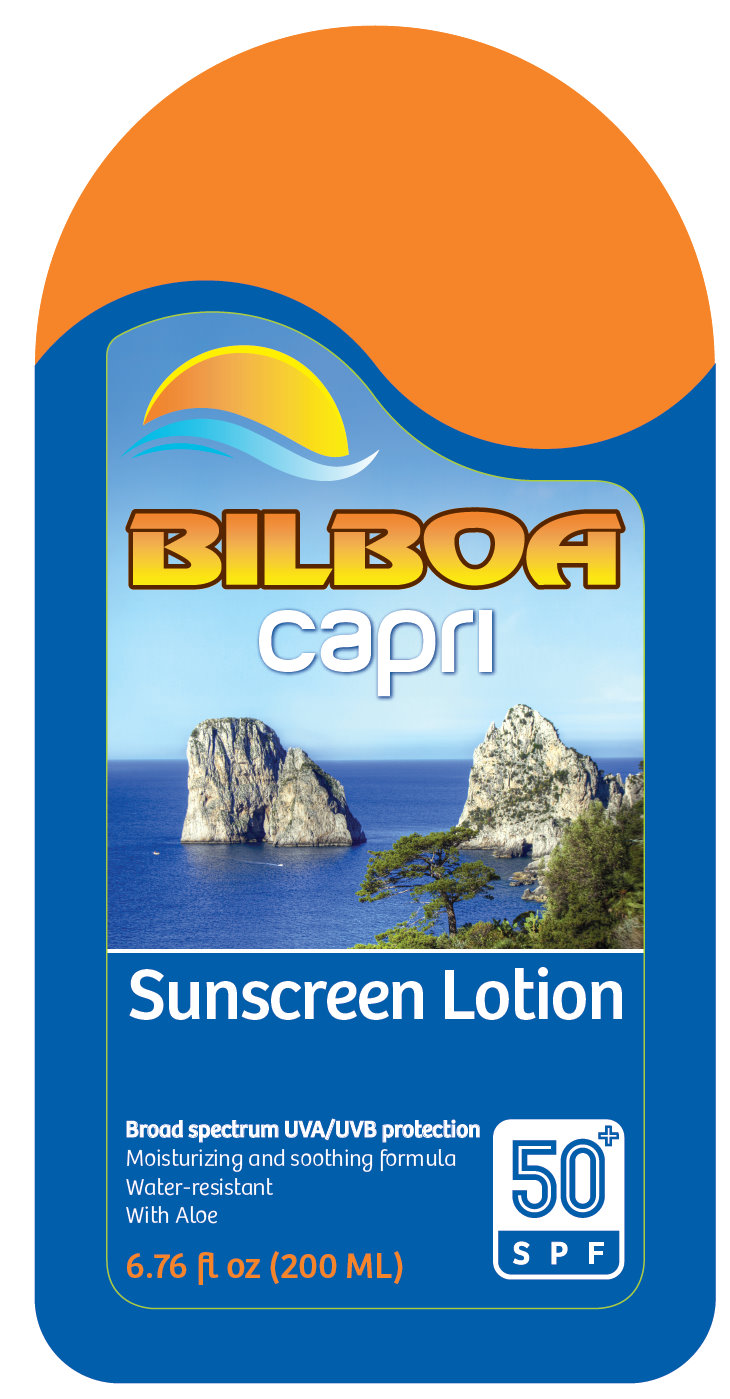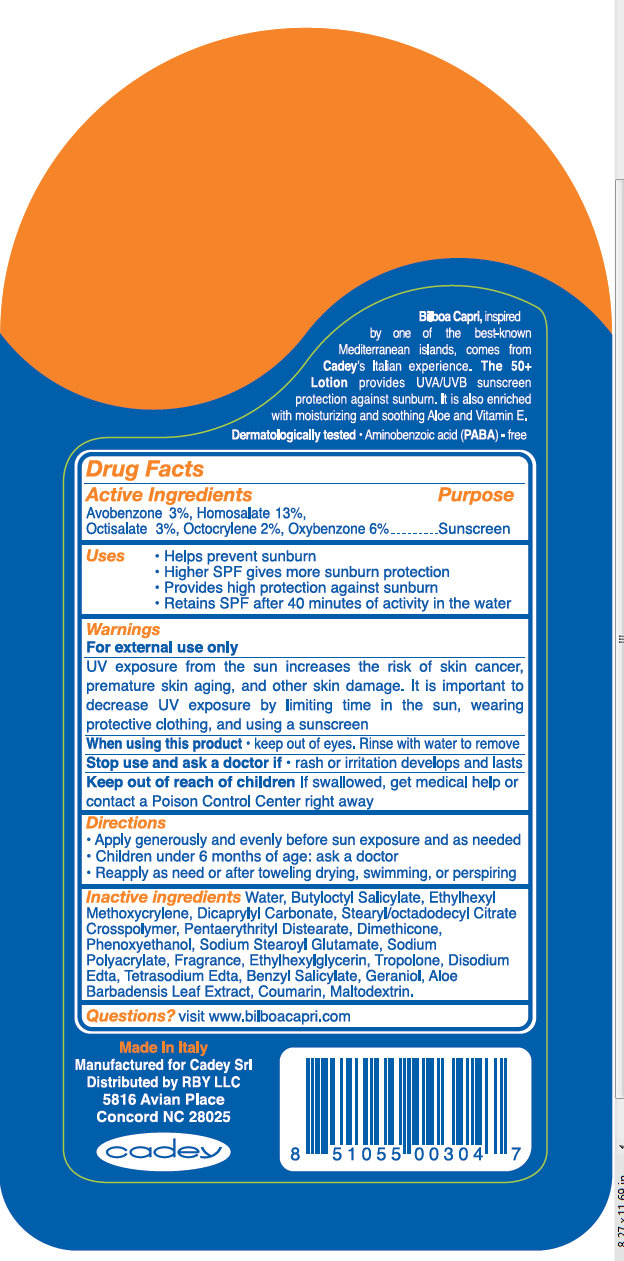 DRUG LABEL: Bilboa Capri Sunscreen SPF 50 Plus
NDC: 76070-120 | Form: LOTION
Manufacturer: Cadey S.r.l.
Category: otc | Type: HUMAN OTC DRUG LABEL
Date: 20110506

ACTIVE INGREDIENTS: AVOBENZONE 3 mL/100 mL; HOMOSALATE 13 mL/100 mL; OCTISALATE 3 mL/100 mL; OCTOCRYLENE 2 mL/100 mL; OXYBENZONE 6 mL/100 mL
INACTIVE INGREDIENTS: WATER; BUTYLOCTYL SALICYLATE; DICAPRYLYL CARBONATE; DIMETHICONE; PHENOXYETHANOL; ETHYLHEXYLGLYCERIN; TROPOLONE; EDETATE DISODIUM; EDETATE SODIUM; BENZYL SALICYLATE; GERANIOL; ALOE VERA LEAF; COUMARIN; MALTODEXTRIN

Bilboa Capri Sunscreen Lotion SPF 50 Plus

Active Ingredients Purpose

Avobenzone 3%, Homosalate 13%,
Octisalate 3%, Octocrylene 2%, Oxybenzone 6% Sunscreen

Uses
- Helps prevent sunburn
- Higher SPF gives more sunburn protection
- Provides high protection against sunburn
- Retains SPF after 40 minutes of activity in the water

Warnings
For external use only

UV exposure from the sun increases the risk of skin cancer, premature skin aging, and other skin damage. It is important to decrease UV exposure by limiting time in the sun, wearing protective clothing, and using a sunscreen

When using this product - keep out of eyes. Rinse with water to remove

Stop use and ask a doctor if - rash or irritation develops and lasts

Keep out of reach of children If swallowed, get medical help or contact a Poison Control Center right away

Directions
- Apply generously and evenly before sun exposure and as needed
- Children under 6 months of age: ask a doctor
- Reapply as need or after toweling drying, swimming, or perspiring

INACTIVE INGREDIENT

Inactive ingredients Water, Butyloctyl Salicylate, Ethylhexyl Methoxycrylene, Dicaprylyl Carbonate, Stearyl/octadodecyl Citrate Crosspolymer, Pentaerythrityl Distearate, Dimethicone, Phenoxyethanol, Sodium Stearoyl Glutamate, Sodium Polyacrylate, Fragrance, Ethylhexylglycerin, Tropolone, Disodium Edta, Tetrasodium Edta, Benzyl Salicylate, Geraniol, Aloe Barbadensis Leaf Extract, Coumarin, Maltodextrin.

Questions? visit www.cadeyusa.com

DESCRIPTION

Bilboa Capri, inspired by one of the best-known Mediterranean islands, comes from Cadey’s Italian experience. The 50+ Lotion provides UVA/UVB sunscreen protection against sunburn. It is also enriched with moisturizes and soothing Aloe and Vitamin E. Dermatologically tested - Aminobenzoic acid (PABA) - free

Made In Italy
Manufactured for Cadey Srl
Distributed by RBY LLC
5816 Avian Place
Concord NC 28025

cadey

PACKAGE LABEL

BILBOA Caprl Sunscreen Lotion Broad spectrum UVA/UVB protection Moisturizing and soothing formula 50+ SPF Water-resistant With Aloe 6.76 fl oz (200 ML) Made In Italy Manufactured for Cadey Srl Distributed by RBY LLC 5816 Avian Place Concord NC 28025 cadey 8 51055 00304 7